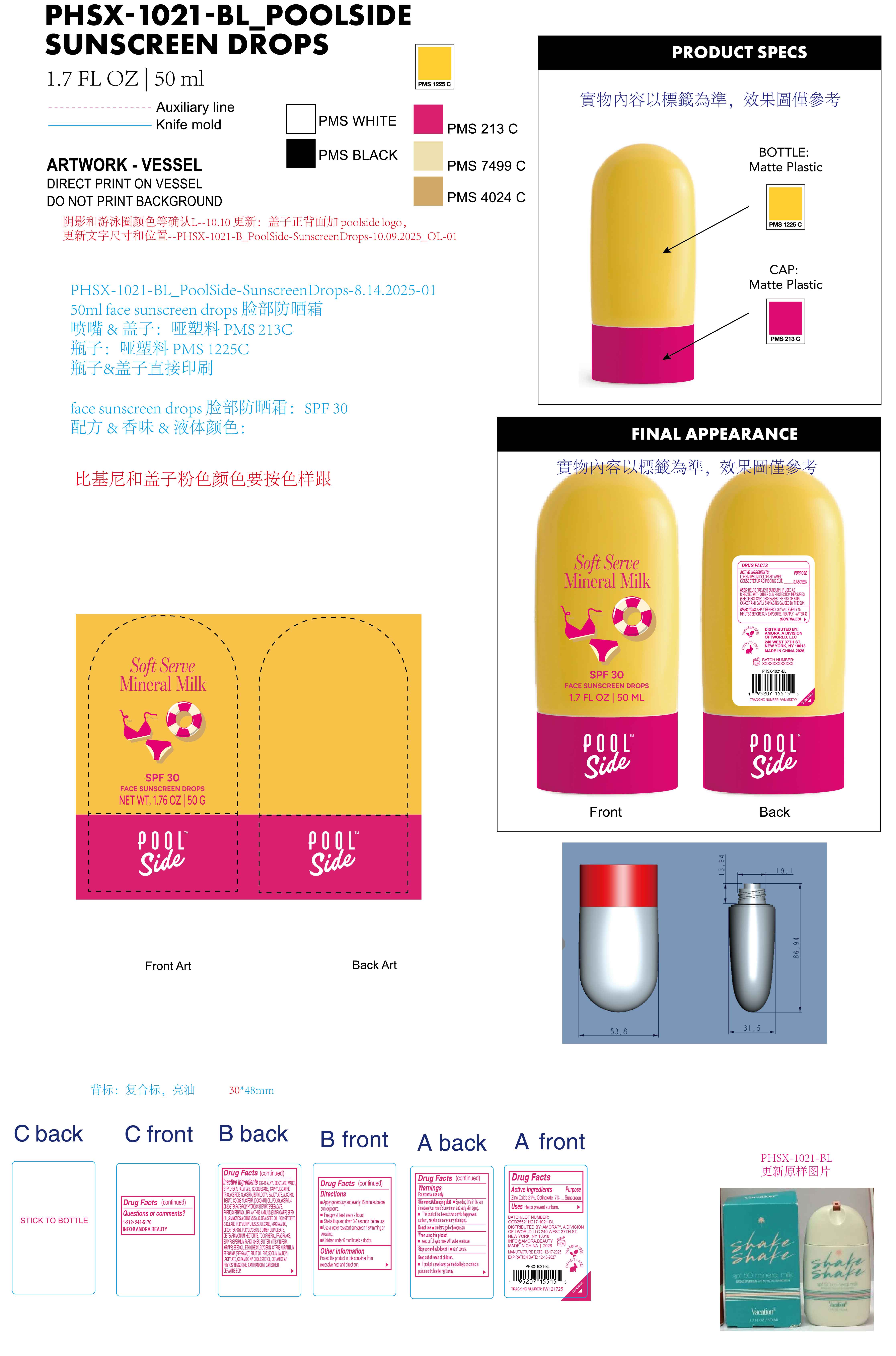 DRUG LABEL: Poolside Soft Serve Mineral Milk  SPF 30 face sunscreen drops
NDC: 85161-135 | Form: LOTION
Manufacturer: Longway Technology(Guangzhou)Co.,Ltd.
Category: otc | Type: HUMAN OTC DRUG LABEL
Date: 20251223

ACTIVE INGREDIENTS: ZINC OXIDE 0.21 g/1 g; OCTINOXATE 0.07 g/1 g
INACTIVE INGREDIENTS: CARBOMER; CERAMIDE 9; BUTYROSPERMUM PARKII (SHEA) BUTTER; HELIANTHUS ANNUUS (SUNFLOWER) SEED OIL; CERAMIDE NP; WATER; SIMMONDSIA CHINENSIS (JOJOBA) SEED OIL; NIACINAMIDE; PHYTOSPHINGOSINE; ETHYLHEXYL PALMITATE; DIISOSTEAROYL POLYGLYCERYL-3 DIMER DILINOLEATE; DISTEARDIMONIUM HECTORITE; ETHYLHEXYLGLYCERIN; COCOS NUCIFERA (COCONUT) OIL; CERAMIDE AP; POLYGLYCERYL-3 OLEATE; VITIS VINIFERA (GRAPE) SEED OIL; XANTHAN GUM; POLYGLYCERYL-4 DIISOSTEARATE/POLYHYDROXYSTEARATE/SEBACATE; POLYMETHYLSILSESQUIOXANE (11 MICRONS); CERAMIDE EOS; BUTYLOCTYL SALICYLATE; BHT; CHOLESTEROL; C12-15 ALKYL BENZOATE; CAPRYLIC/CAPRIC TRIGLYCERIDE; ALCOHOL; FRAGRANCE 13576; CITRUS AURANTIUM BERGAMIA (BERGAMOT) FRUIT OIL; TOCOPHEROL; ISODODECANE; GLYCERIN; PHENOXYETHANOL; SODIUM LAUROYL LACTYLATE

ACTIVE INGREDIENT

Zinc Oxide 21%, Octinoxate 7%

KEEP OUT OF REACH OF CHILDREN

If product is swallowed get medical help or contact a poison control center night away.

INDICATIONS AND USAGE

Helps prevent sunburn.

OTHER SAFETY INFORMATION

Protect the product in this container from excessive heat and direct sun.

QUESTIONS

1-212-244-5170

INFO@AMORA.BEAUTY

Warnings

For external use only.

Skin cancer/skin aging alert .

Spending time in the sun increases your risk of skin cancer and early skin aging.

This product has been shown only to help prevent sunburn, not skin cancer or early skin aging.

Do not use m on damaged or broken skin.

When using this product keep out of eyes. rinse with water to remove.

Stop use and ask doctor if rash occurs.

Keep out of reach of children.If product is swallowed get medical help or contact a poison center center night away,

Directions

Apply generously and evenly 15 minutes before sun exposure.

Reapply at least every 2 hours.

Shake it up and down 3-5 seconds before use.

Use a water resistant sunscreen if swimming or sweating.

Children under 6 month: ask a doctor.

INACTIVE INGREDIENT

C12-15 ALKYL BENZOATE, WATER, ETHYLHEXYL PALMITATE, ISODODECANE, CAPRYLIC/CAPRIC TRIGLYCERIDE, GLYCERIN, BUTYLOCTYL SALICYLATE, ALCOHOL DENAT., COCOS NUCIFERA (COCONUT) OIL, POLYGLYCERYL-4 DIISOSTEARATE/POLYHYDROXYSTEARATE/SEBACATE, PHENOXYETHANOL, HELIANTHUS ANNUUS (SUNFLOWER) SEED OIL, SIMMONDSIA CHINENSIS (JOJOBA) SEED OIL, POLYGLYCERYL-3 OLEATE, POLYMETHYLSILSESQUIOXANE, NIACINAMIDE, DIISOSTEAROYL POLYGLYCERYL-3 DIMER DILINOLEATE, DISTEARDIMONIUM HECTORITE, TOCOPHEROL, FRAGRANCE, BUTYROSPERMUM PARKII (SHEA) BUTTER, VITIS VINIFERA (GRAPE) SEED OIL, ETHYLHEXYLGLYCERIN, CITRUS AURANTIUM BERGAMIA (BERGAMOT) FRUIT OIL, BHT, SODIUM LAUROYL LACTYLATE, CERAMIDE NP, CHOLESTEROL, CERAMIDE AP, PHYTOSPHINGOSINE, XANTHAN GUM, CARBOMER, CERAMIDE EOP

PURPOSE

Sunscreen